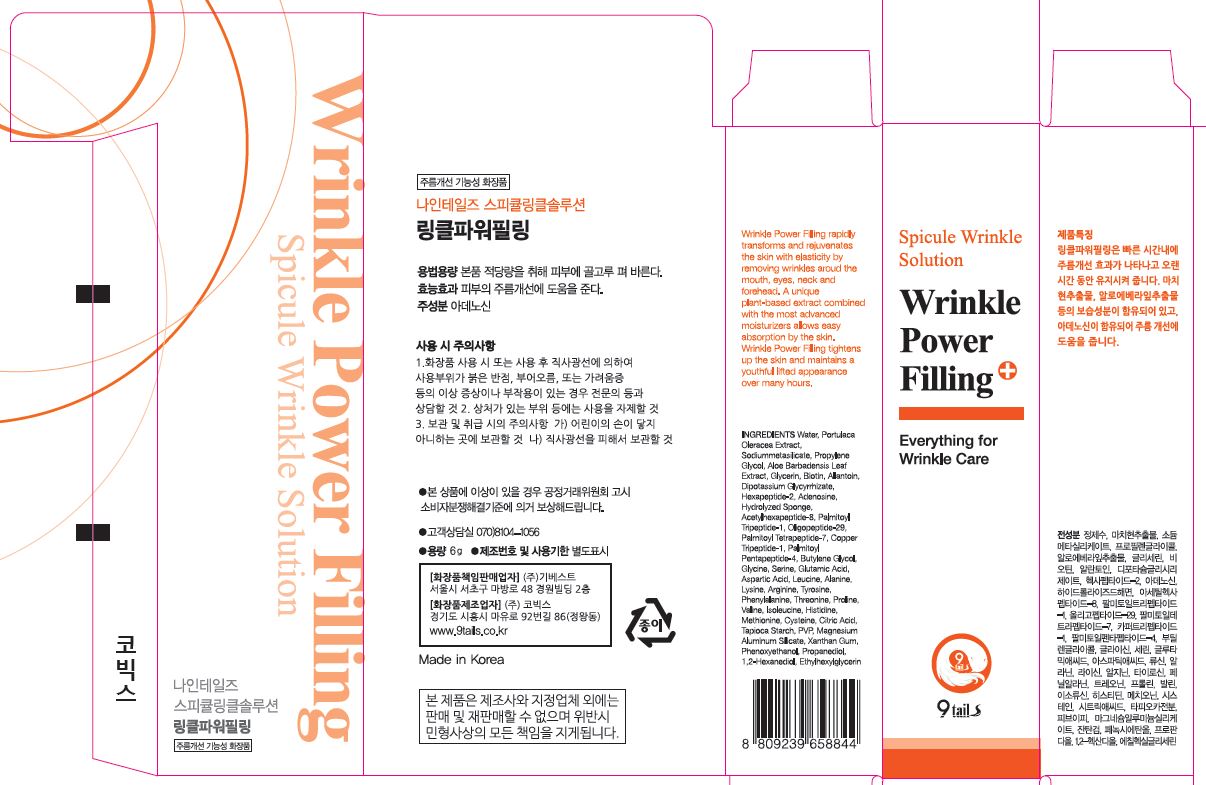 DRUG LABEL: Wrinkle Power Filling
NDC: 72176-0100 | Form: GEL
Manufacturer: GIBEST
Category: otc | Type: HUMAN OTC DRUG LABEL
Date: 20200813

ACTIVE INGREDIENTS: GLYCERIN 3.55 g/100 mL
INACTIVE INGREDIENTS: WATER; ADENOSINE

ACTIVE INGREDIENT

Glycerin

INACTIVE INGREDIENT

Water, Propylene Glycol, Biotin, Aloe Barbadensis Leaf Extract, Adenosine, Allantoin, etc.

PURPOSE

Skin protectant - Wrinkle Care

keep out or reach of the children

INDICATIONS AND USAGE

[How to Use]

1. Towel dry after face washing.
2. Apply thin layer to the direction of wrinkle. Keep patting gently for about 15 seconds.
3. Try not to talk or move for at least 2 minutes until dry.
4. Strain feeling of your skin will disappear naturally.

- Shake well before you use.
- The nature of Hydrolyzed Sponge, it may be pricking little bit depends on individual's skin condition. However, it is quite natural and proving for working to your skin.

WARNINGS

[Caution]

1. Use only directed.
2. Avoid stroing in extremely high or low temperatures and areas exposed to direct sunlight.
3. If irritation occurs, discontinue use.

DOSAGE AND ADMINISTRATION

for external use only